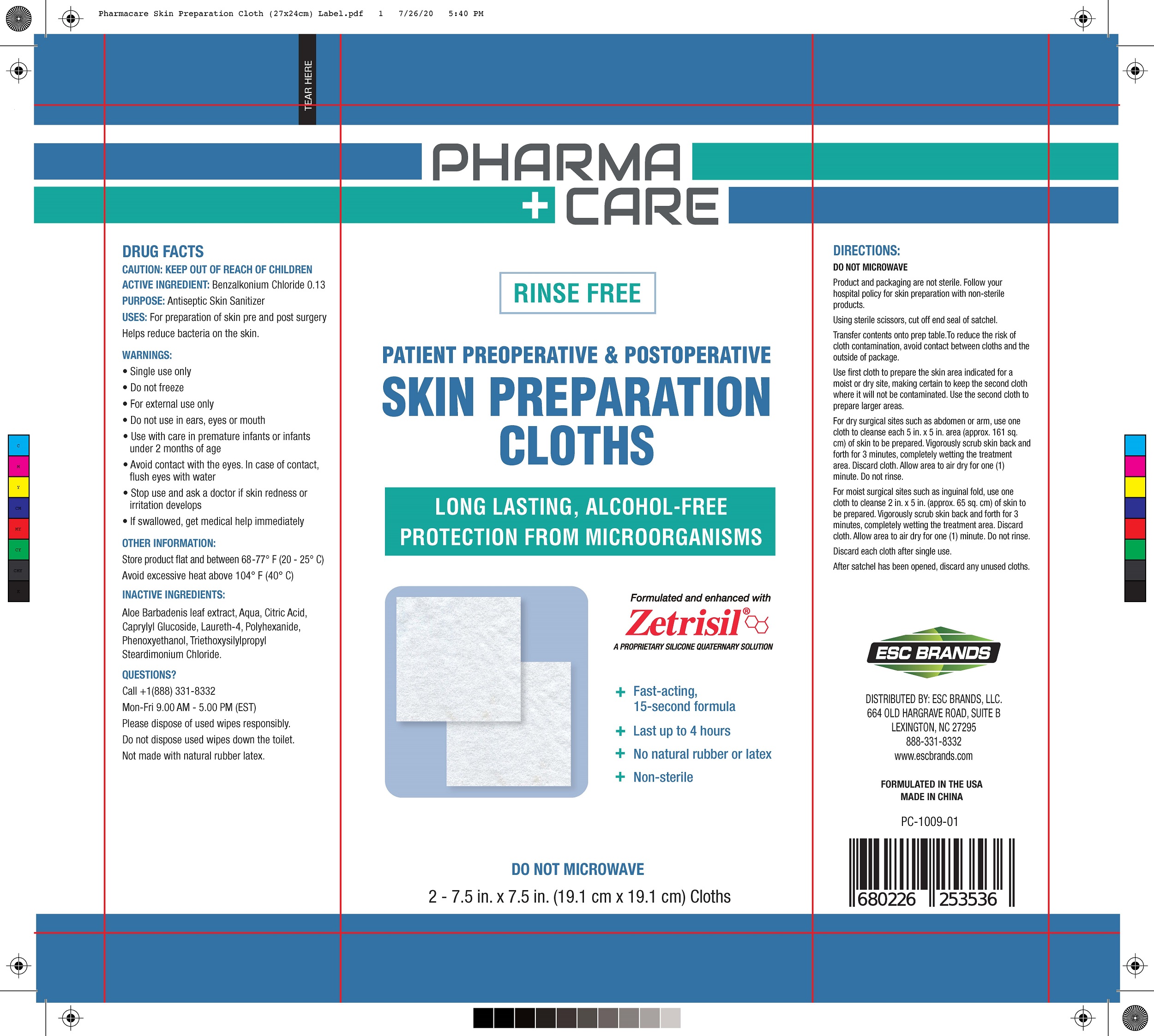 DRUG LABEL: Skin Preparation
NDC: 51706-962 | Form: CLOTH
Manufacturer: Landy International
Category: otc | Type: HUMAN OTC DRUG LABEL
Date: 20201201

ACTIVE INGREDIENTS: BENZALKONIUM CHLORIDE 0.13 g/100 g
INACTIVE INGREDIENTS: PHENOXYETHANOL; LAURETH-4; CAPRYLYL GLUCOSIDE; POLIHEXANIDE; TRIETHOXYSILYLPROPYL STEARDIMONIUM CHLORIDE; WATER; ALOE VERA LEAF; CITRIC ACID MONOHYDRATE

51706-962 Skin Preparation Cloth 0.13% Benzalkonium chloride

Active Ingredient(s)

Benzalkonium Chloride 0.13%

Purpose

Antiseptic Skin Sanitizer

Use

For preparation of skin pre and post surgery
Helps reduce bacteria on the skin.

Warnings

• Single use only
• Do not freeze
• For external use only
• Do not use in ears, eyes or mouth
• Use with care in premature infants or infants
under 2 months of age
• Avoid contact with the eyes. In case of contact,
flush eyes with water
• Stop use and ask a doctor if skin redness or
irritation develops
• If swallowed, get medical help immediately

Keep out of reach of children

Directions

DO NOT MICROWAVE
Product and packaging are not sterile. Follow your
hospital policy for skin preparation with non-sterile
products.
Using sterile scissors, cut off end seal of satchel.
Transfer contents onto prep table.To reduce the risk of
cloth contamination, avoid contact between cloths and the
outside of package.
Use first cloth to prepare the skin area indicated for a
moist or dry site, making certain to keep the second cloth
where it will not be contaminated. Use the second cloth to
prepare larger areas.
For dry surgical sites such as abdomen or arm, use one
cloth to cleanse each 5 in. x 5 in. area (approx. 161 sq.
cm) of skin to be prepared. Vigorously scrub skin back and
forth for 3 minutes, completely wetting the treatment
area. Discard cloth. Allow area to air dry for one (1)
minute. Do not rinse.
For moist surgical sites such as inguinal fold, use one
cloth to cleanse 2 in. x 5 in. (approx. 65 sq. cm) of skin to
be prepared. Vigorously scrub skin back and forth for 3
minutes, completely wetting the treatment area. Discard
cloth. Allow area to air dry for one (1) minute. Do not rinse.
Discard each cloth after single use.
After satchel has been opened, discard any unused cloths.

Other information

Store product flat and between 68 -77° F (20 - 25° C)
Avoid excessive heat above 104° F (40° C)

Inactive ingredients

Aloe Barbadenis leaf extract, Aqua, Citric Acid,
Caprylyl Glucoside, Laureth-4, Polyhexanide,
Phenoxyethanol, Triethoxysilylpropyl
Steardimonium Chloride.